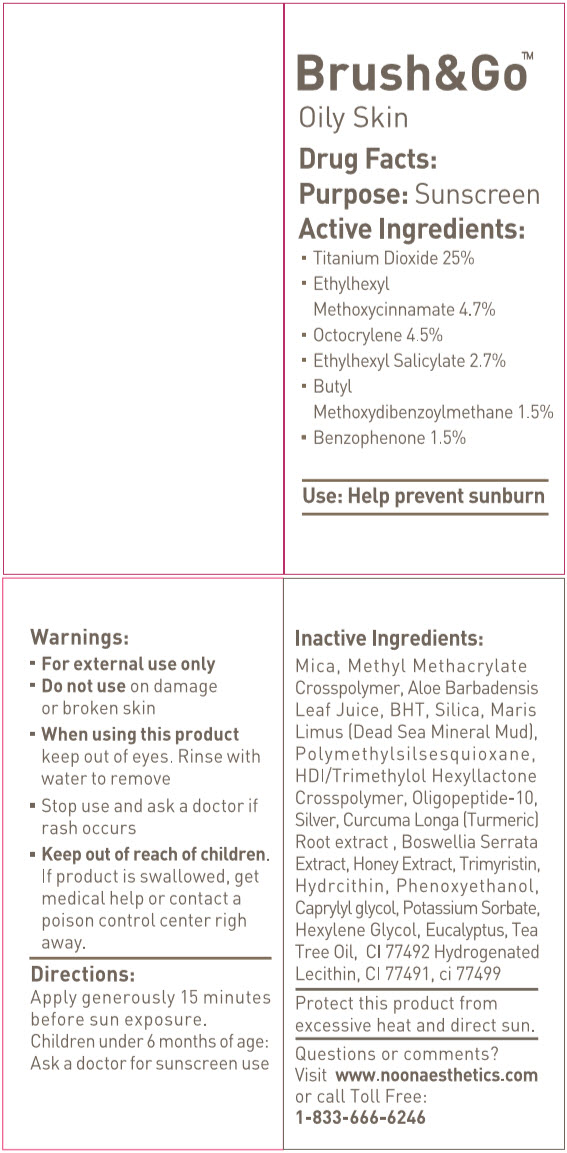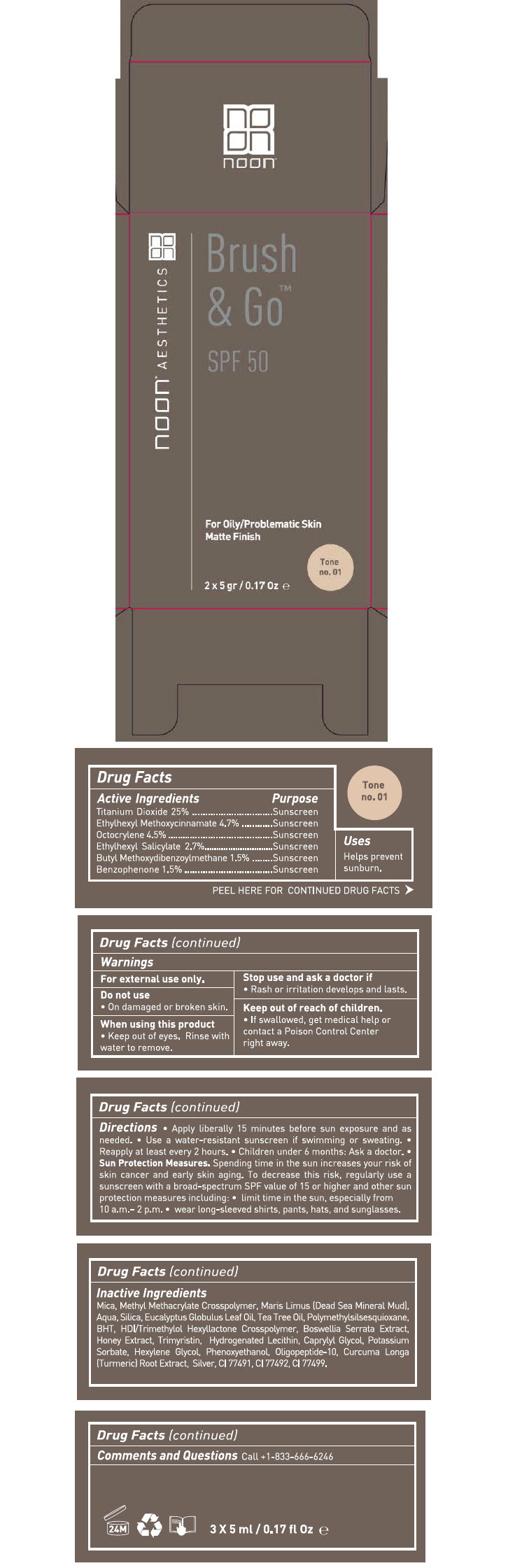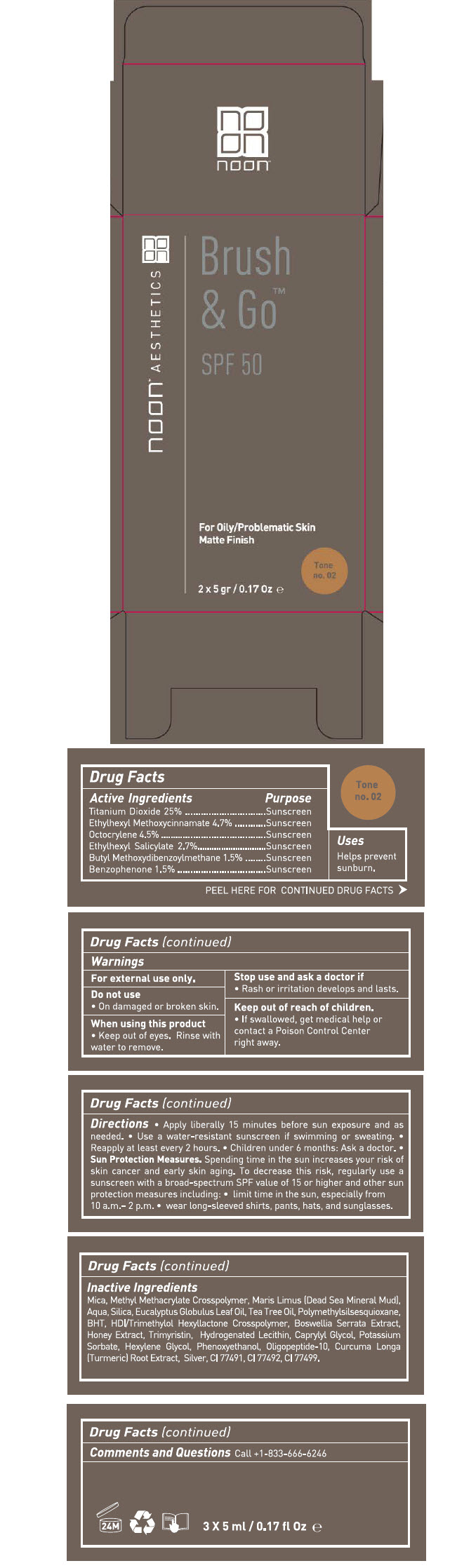 DRUG LABEL: Brush and Go 
NDC: 78863-1012 | Form: POWDER
Manufacturer: Noon Aesthetics M.R. Ltd
Category: otc | Type: HUMAN OTC DRUG LABEL
Date: 20250113

ACTIVE INGREDIENTS: Titanium Dioxide 1.25 g/5 g; Octinoxate 0.236 g/5 g; Octocrylene 0.225 g/5 g; Octisalate 0.135 g/5 g; Avobenzone 0.075 g/5 g; Oxybenzone 0.075 g/5 g
INACTIVE INGREDIENTS: MICA; METHYL METHACRYLATE/GLYCOL DIMETHACRYLATE CROSSPOLYMER; BUTYLATED HYDROXYTOLUENE; Silicon Dioxide; FERRIC OXIDE YELLOW; HYDROGENATED SOYBEAN LECITHIN; FERRIC OXIDE RED; FERROSOFERRIC OXIDE; Polymethylsilsesquioxane (4.5 Microns); HEXAMETHYLENE DIISOCYANATE/TRIMETHYLOL HEXYLLACTONE CROSSPOLYMER; Oligopeptide-10; Silver; TURMERIC; INDIAN FRANKINCENSE; Honey; Trimyristin; Phenoxyethanol; Caprylyl Glycol; Potassium Sorbate; Hexylene Glycol; Eucalyptus Gum; Tea Tree oil

Brush and Go™
Oily Problematic Skin

Drug Facts

Active Ingredients

Titanium Dioxide 25%
Ethylhexyl Methoxycinnamate 4.7%
Octocrylene 4.5%
Ethylhexyl Salicylate 2.7%
Butyl Methoxydibenzoylmethane 1.5%
Benzophenone 1.5%

Purpose

Sunscreen

Use

Help prevent sunburn

Warnings

For external use only

Do not use on damage or broken skin

When using this product keep out of eyes. Rinse with water to remove

Stop use and ask a doctor if rash occurs

Keep out of reach of children. If product is swallowed, get medical help or contact a poison control center right away.

Directions

Apply generously 15 minutes before sun exposure.

Children under 6 months of age: Ask a doctor for sunscreen use

Inactive Ingredients

Mica, Methyl Methacrylate Crosspolymer, Aloe Barbadensis Leaf Juice, BHT, Silica, Maris Limus (Dead Sea Mineral Mud), Polymethylsilsesquioxane, HDI/Trimethylol Hexyllactone Crosspolymer, Oligopeptide-10,Silver, Curcuma Longa (Turmeric) Root extract , Boswellia Serrata Extract, Honey Extract, Trimyristin, Hydrogenated Lecithin, Phenoxyethanol, Caprylyl glycol, Potassium Sorbate, Hexylene Glycol, Eucalyptus, Tea Tree Oil, CI 77492,Hydrogenated Lecithin, CI 77491, ci 77499.

Other information

Protect this product from excessive heat and direct sun.

Questions or comments?

Visit www.noonaesthetics.com or call toll free1-833-666-6246

PRINCIPAL DISPLAY PANEL - 5 g Bottle Label

Brush&Go™

Oily Skin

Drug Facts:
Purpose: Sunscreen
Active Ingredients:

- Titanium Dioxide 25%
- Ethylhexyl
  Methoxycinnamate 4.7%
- Octocrylene 4.5%
- Ethylhexyl Salicylate 2.7%
- Butyl
  Methoxydibenzoylmethane 1.5%
- Benzophenone 1.5%

Use: Help prevent sunburn

PRINCIPAL DISPLAY PANEL - 5 gr Bottle Carton - Tone no. 01

noon™ AESTHETICS

Brush
& Go™

SPF 50

For Oily/Problematic Skin
Matte Finish

Tone
no. 01

2 x 5 gr / 0.17 Oz ℮

PRINCIPAL DISPLAY PANEL - 5 gr Bottle Carton - Tone no. 02

noon™ AESTHETICS

Brush
& Go™

SPF 50

For Oily/Problematic Skin
Matte Finish

Tone
no. 02

2 x 5 gr / 0.17 Oz ℮